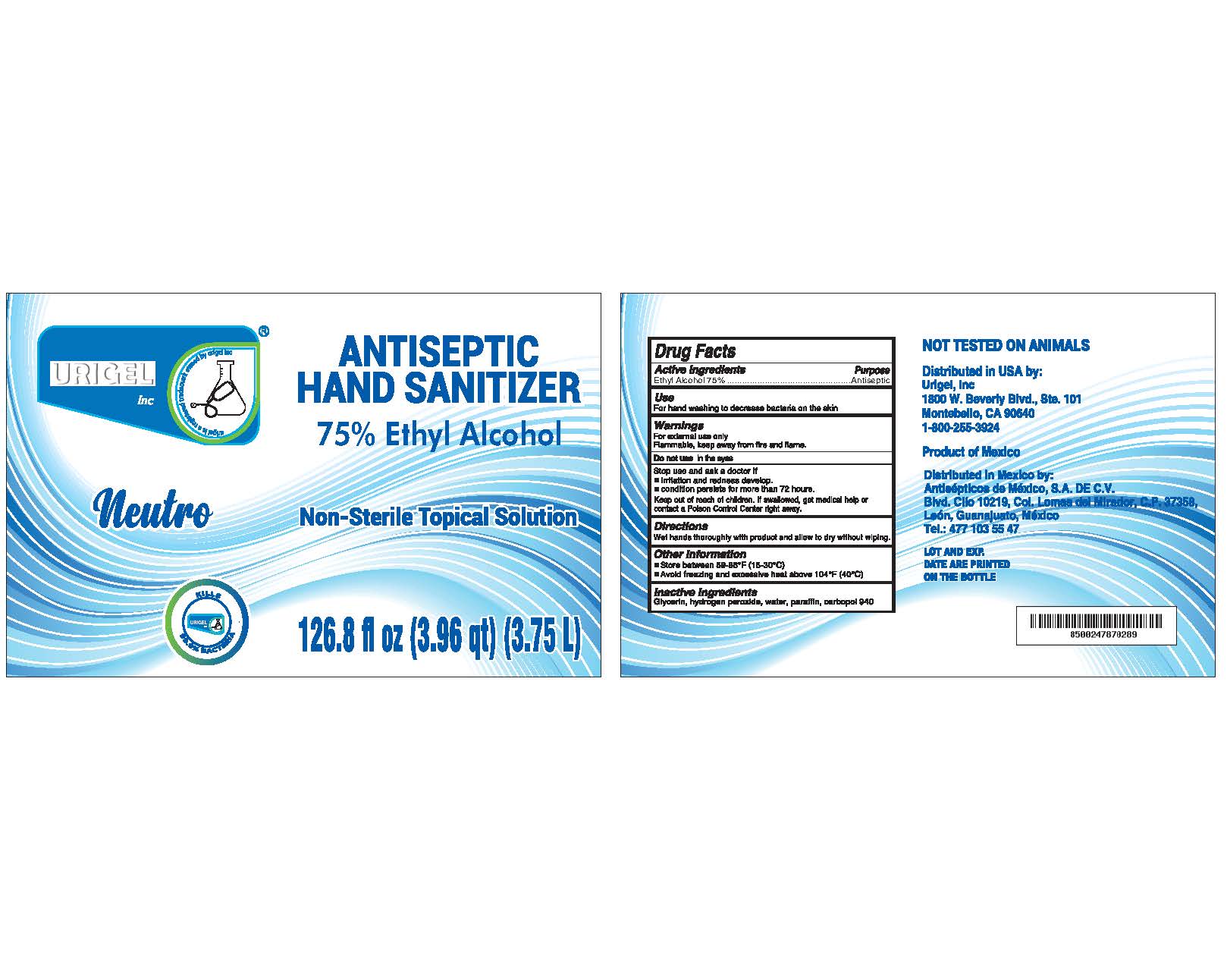 DRUG LABEL: Urigel Neutro Antiseptic Hand Sanitize 75%r 75%
NDC: 80924-003 | Form: GEL
Manufacturer: Urigel Inc.
Category: otc | Type: HUMAN OTC DRUG LABEL
Date: 20210208

ACTIVE INGREDIENTS: ALCOHOL 0.75 mL/1 mL
INACTIVE INGREDIENTS: GLYCERIN; HYDROGEN PEROXIDE; WATER; PARAFFIN

Urigel Neutro Antiseptic Hand Sanitizer 75%

Active ingredient

Ethyl Alcohol 75%

Purpose

Antiseptic

Use

For hand washing to decrease bacteria on the skin

Warnings

For external use only.
Flammable, keep away from fire and flame.

Do not use

in the eyes.

Stop use and ask a doctor if:

- irritation and redness develop.
- condition persists for more than 72 hours.

Keep out of reach of children.

If swallowed, get medical help or contact a Poison Control Center right away.

Directions

Wet hands thoroughly with product and allow to dry without wiping.

Other information

- Store between 59-86°F (15-30°C)
- Avoid freezing and excessive heat above 104°F (40°C)

Inactive ingredients

Glycerin, hydrogen peroxide, water, paraffin, carbopol 940

Package Labeling:

3.75ML/! Gal NDC 80924-0 03-10